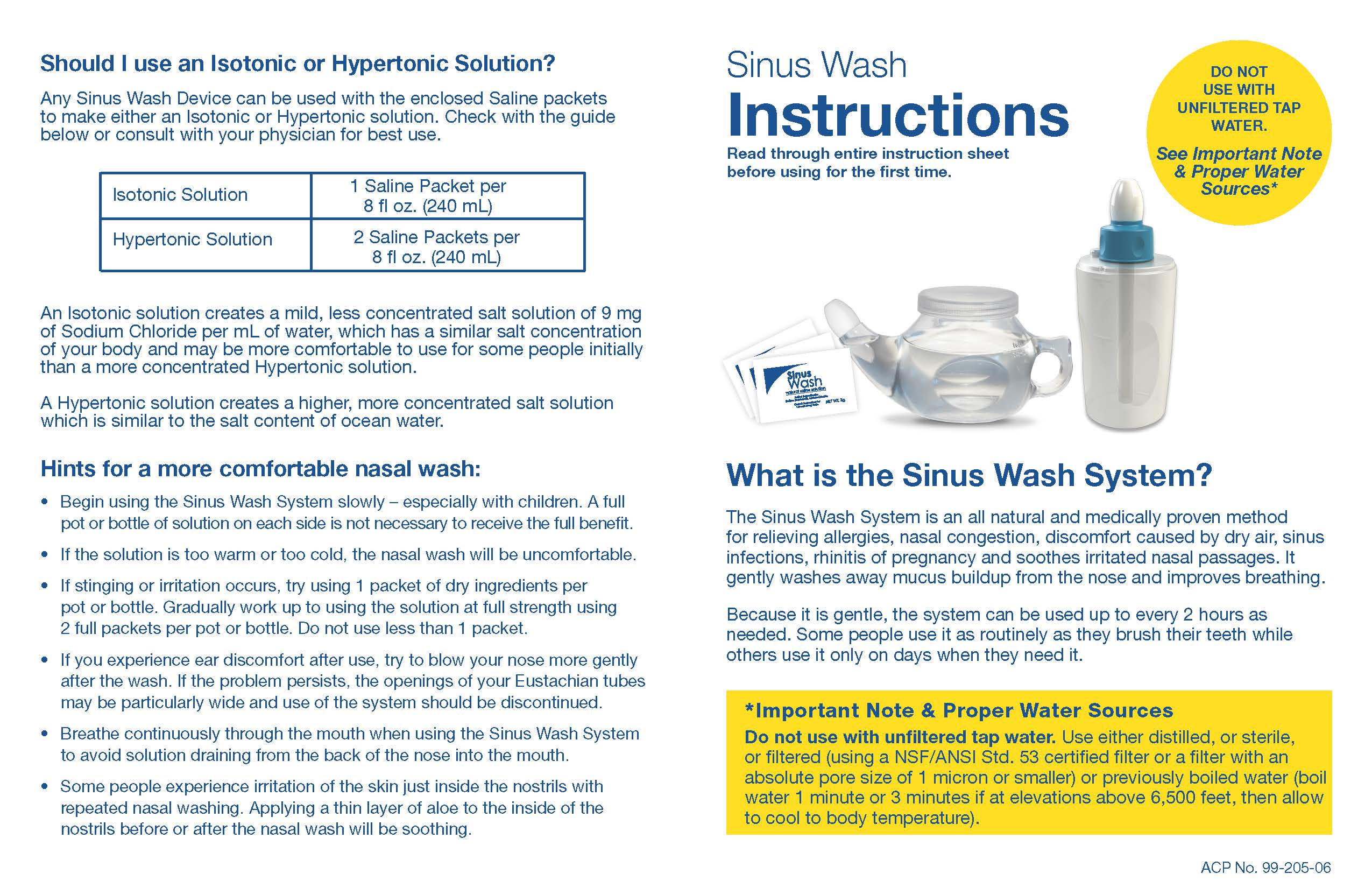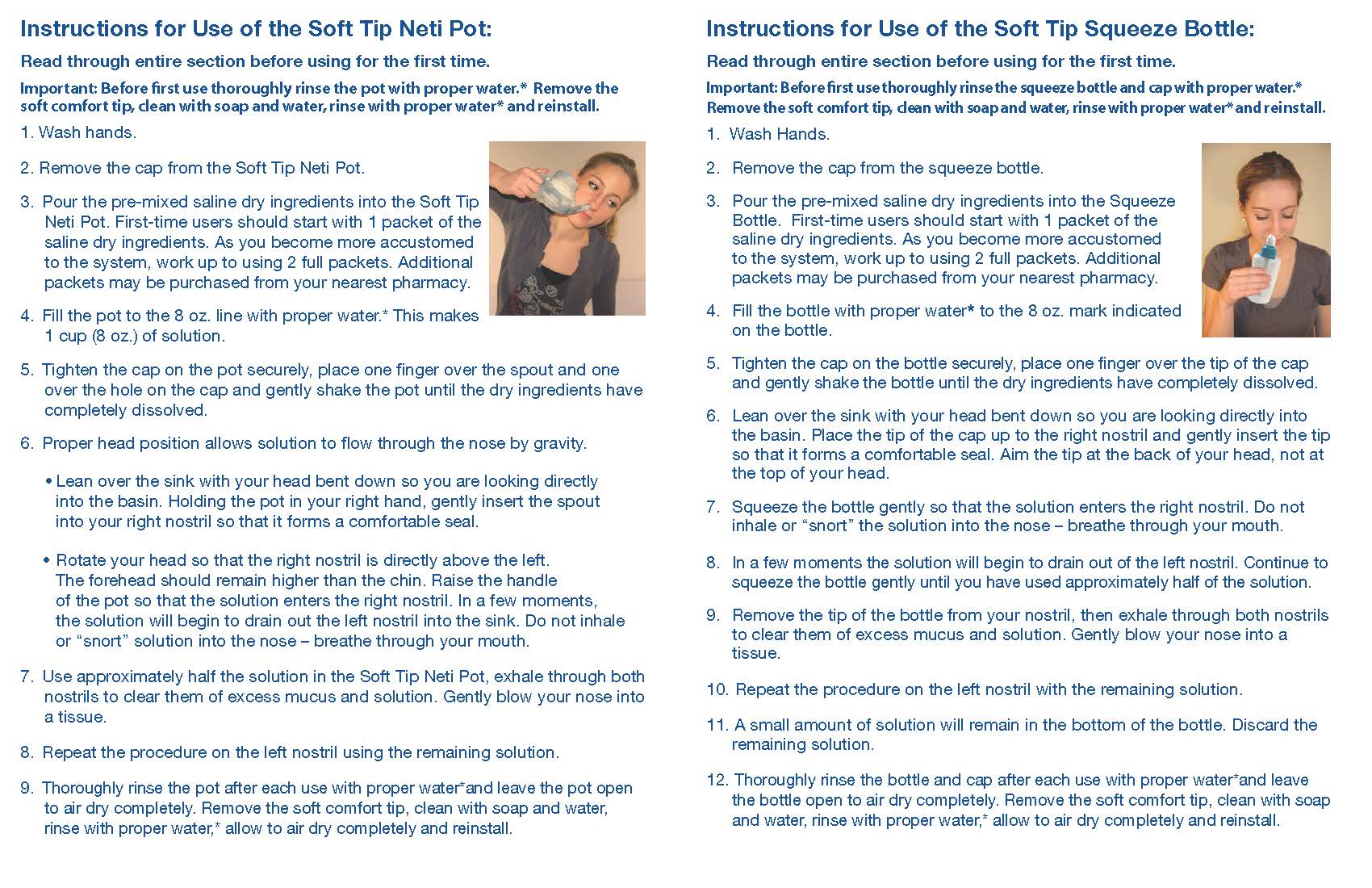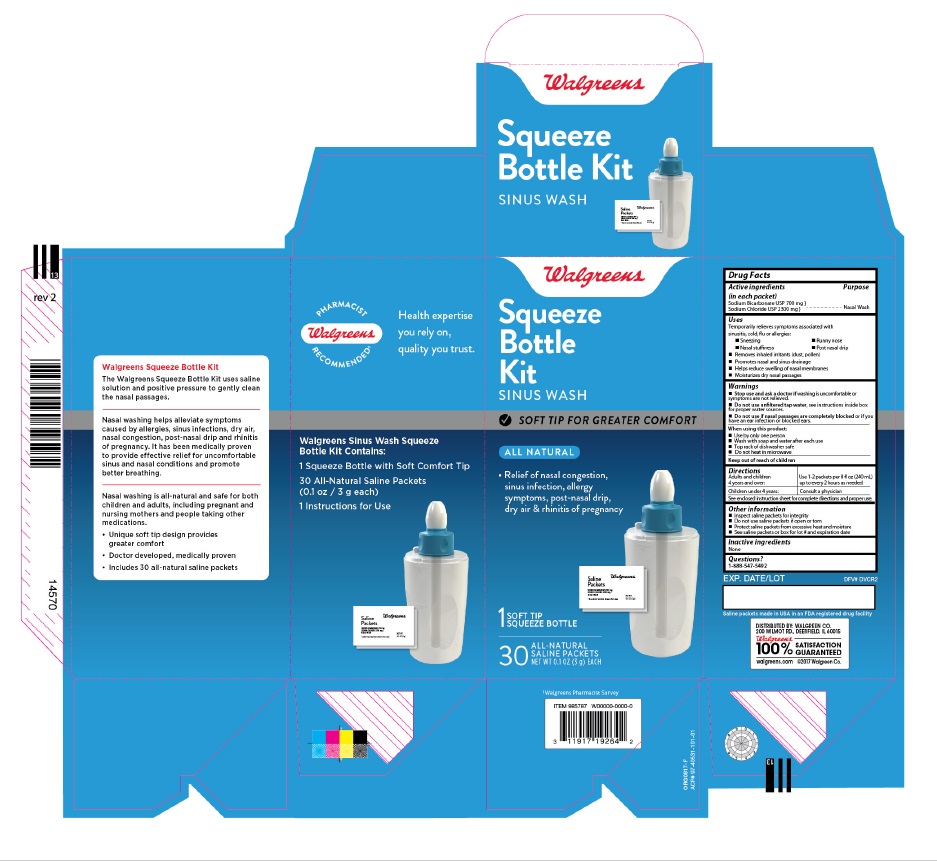 DRUG LABEL: Walgreens Sinus Wash Squeeze Bottle Kit
NDC: 0363-1405 | Form: KIT | Route: NASAL
Manufacturer: Walgreen Company
Category: otc | Type: HUMAN OTC DRUG LABEL
Date: 20250429

ACTIVE INGREDIENTS: SODIUM BICARBONATE 700 mg/3000 mg; SODIUM CHLORIDE 2300 mg/3000 mg
INACTIVE INGREDIENTS: WATER

Active ingredients

(in each packet)

Sodium Bicarbonate USP 700 mg

Sodium Chloride USP 2300 mg

Purpose

Nasal Wash

Uses

Temporarily relieves symptoms associated with

sinusitis, cold, flu or allergies:

•Sneezing •Runny nose

•Nasal stuffiness •Post nasal drip

•Removes inhaled irritants (dust, pollen)

•Promotes nasal and sinus drainage

•Helps reduce swelling of nasal membranes

•Moisturizes dry nasal passages

Warnings

• Stop use and ask a doctor ifwashing is uncomfortable or

symptoms are not relieved

• Do not use unfiltered tap water, see instructions inside box

for proper water sources.

• Do not use if nasal passages are completely blockedor if you

have an ear infection or blocked ears.

When using this product:

Use by only one person
Wash with soap and water after each use
Top rack of dishwasher safe
Do not heat in microwave

Keep out of reach of children.

DOSAGE AND ADMINISTRATION

Directions; Adults and children; 4 years and over: | Use 1-2 packetsper 8 fl oz (240 mL); up to every 2 hours as needed
Children under 4 years: | Consult a physician

See enclosed instruction sheet for complete directions and proper use

Other information

- Inspect saline packets for integrity
- Dp not use saline packets if open or torn
- Protect saline packets from excessive heat and moisture
- See saline packets or box for lot # and expiration date

Inactive ingredients

None

Questions?

1-888-547-5492